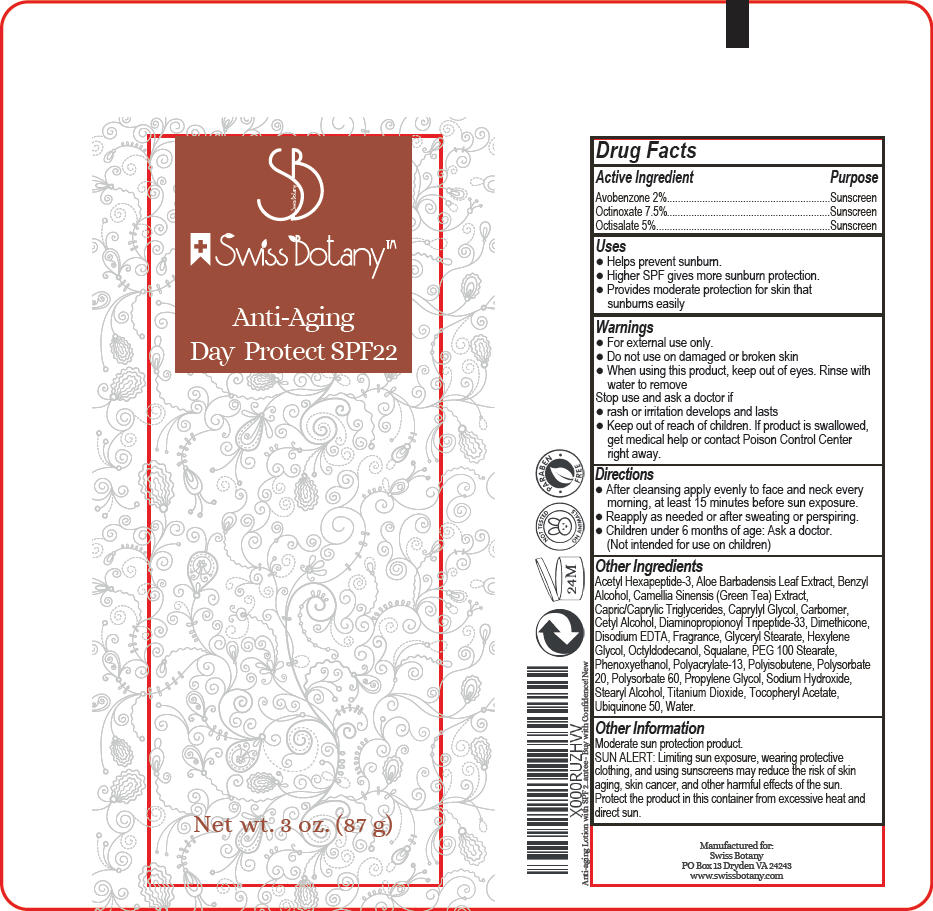 DRUG LABEL: Anti-Aging Day Protect SPF 22
NDC: 70048-001 | Form: LOTION
Manufacturer: Swiss Botany
Category: otc | Type: HUMAN OTC DRUG LABEL
Date: 20150904

ACTIVE INGREDIENTS: Octinoxate 75 mg/1 g; Octisalate 50 mg/1 g; Avobenzone 20 mg/1 g
INACTIVE INGREDIENTS: Acetyl Hexapeptide-8; Aloe; Benzyl Alcohol; Ascorbic Acid; Green Tea Leaf; Tricaprin; Tricaprylin; Caprylyl Glycol; Carbomer Homopolymer Type C (Allyl Pentaerythritol Crosslinked) ; Cetyl Alcohol; Dimethicone; Edetate Sodium; Polyisobutylene (1000 MW); Polysorbate 60; Stearyl Alcohol; Glyceryl Monostearate; Hexylene Glycol; Octyldodecanol; Squalane; Peg-100 Stearate; Phenoxyethanol; Polysorbate 20; Propylene Glycol; Sodium Hydroxide; .Alpha.-Tocopherol Acetate; Titanium Dioxide; Water

Anti-Aging Day Protect SPF 22

Drug Facts

ACTIVE INGREDIENT

Active Ingredient | Purpose
Avobenzone 2% | Sunscreen
Octinoxate 7.5% | Sunscreen
Octisalate 5% | Sunscreen

Uses

- Helps prevent sunburn.
- Higher SPF gives more sunburn protection.
- Provides moderate protection for skin that sunburns easily

Warnings

- For external use only.

- Do not use on damaged or broken skin

- When using this product, keep out of eyes. Rinse with water to remove

Stop use and ask a doctor if

- rash or irritation develops and lasts

- Keep out of reach of children. If product is swallowed, get medical help or contact Poison Control Center right away.

Directions

- After cleansing apply evenly to face and neck every morning, at least 15 minutes before sun exposure.
- Reapply as needed or after sweating or perspiring.
- Children under 6 months of age: Ask a doctor. (Not intended for use on children)

Other Ingredients

Acetyl Hexapeptide-3, Aloe Barbadensis Leaf Extract, Benzyl Alcohol, Camellia Sinensis (Green Tea) Extract, Capric/Caprylic Triglycerides, Caprylyl Glycol, Carbomer, Cetyl Alcohol, Diaminopropionoyl Tripeptide-33, Dimethicone, Disodium EDTA, Fragrance, Glyceryl Stearate, Hexylene Glycol, Octyldodecanol, Squalane, PEG 100 Stearate, Phenoxyethanol, Polyacrylate-13, Polyisobutene, Polysorbate 20, Polysorbate 60, Propylene Glycol, Sodium Hydroxide, Stearyl Alcohol, Titanium Dioxide, Tocopheryl Acetate, Ubiquinone 50, Water.

Other Information

Moderate sun protection product.

SUN ALERT

Limiting sun exposure, wearing protective clothing, and using sunscreens may reduce the risk of skin aging, skin cancer, and other harmful effects of the sun.

Protect the product in this container from excessive heat and direct sun.

PRINCIPAL DISPLAY PANEL - 87 g Tube Label

SB

+Swiss Botany™

Anti-Aging
Day Protect SPF22

Net wt. 3 oz. (87 g)